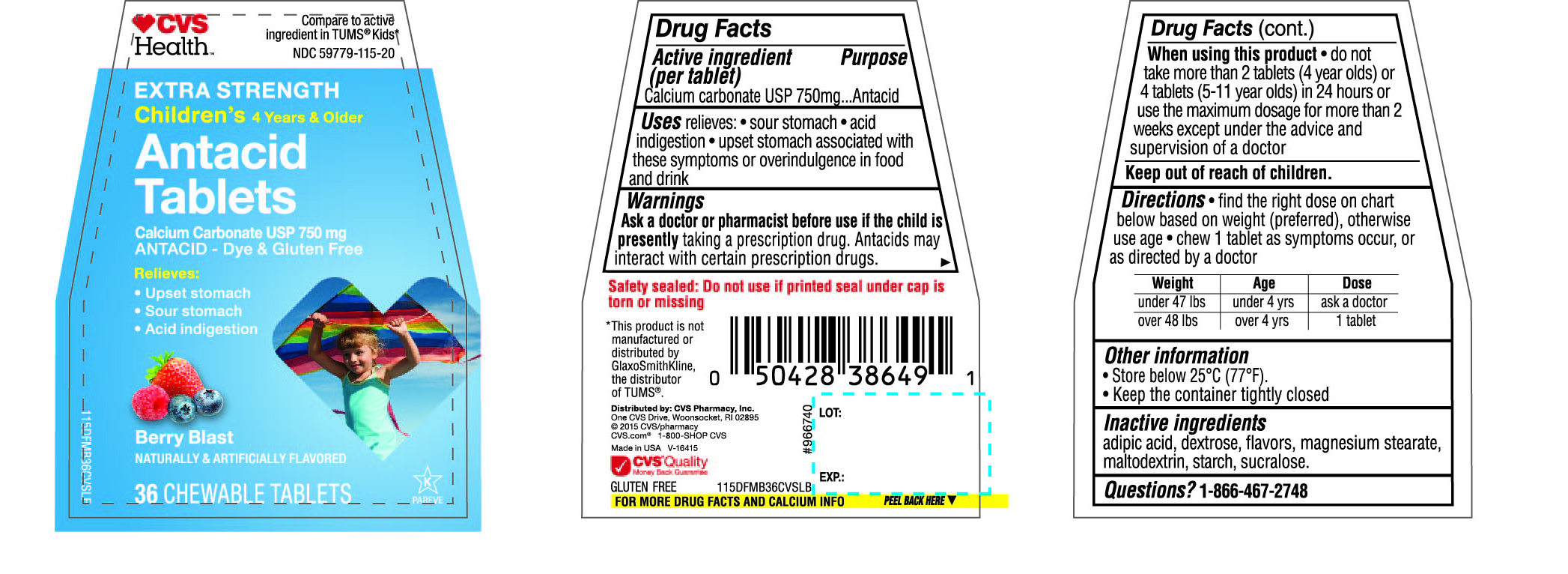 DRUG LABEL: Childrens Antacid Extra Strength
NDC: 69842-015 | Form: TABLET, CHEWABLE
Manufacturer: CVS Pharmacy,Inc
Category: otc | Type: HUMAN OTC DRUG LABEL
Date: 20170320

ACTIVE INGREDIENTS: CALCIUM CARBONATE 750 mg/1 1
INACTIVE INGREDIENTS: ADIPIC ACID; DEXTROSE; MAGNESIUM STEARATE; MALTODEXTRIN; STARCH, CORN; SUCRALOSE

CVS Health Children’s Antacid Tablets Extra Strength Berry Blast 36 Chewable Tablets

Active ingredient (per tablet)

Calcium carbonate USP 750mg

Purpose

Antacid

Uses

relieves :

- sour stomach
- acid indigestion
- upset stomach associated with these symptoms or overindulgence in food and drink

Warnings

Ask a doctor or pharmacist before use if the child is presently taking a prescription drug. Antacids may interact with certain prescription drugs.

When using this product

do not take more than 2 tablets(4 year olds) or 4 tablets (5-11 year olds) in 24 hours or use the maximum dosage for more than 2 weeks except under the advice and supervision of a doctor

Directions

find the right dose on chart below based on weight (preferred), otherwise use age.
chew 1 tablet as symptoms occur, or as directed by a doctor

Weight | Age | Dose
under 47 lbs | under 4 yrs | ask a doctor
over 48 lbs | over 4 yrs | 1 tablet

Other information

Store below 25°C (77°F).
Keep the container tightly closed

Inactive ingredients

adipic acid, dextrose, flavors, magnesium stearate, maltodextrin, starch, sucralose

Questions?

1-866-467-2748

Safety sealed: Do not use if printed seal under cap is torn or missing

Package/Label Principal Display Panel

CVS Health™

Compare to active ingredient in TUMS® Kids*

NDC 69842-015-36

EXTRA STRENGTH

Children’s 4 years & older

Antacid Tablets

Calcium Carbonate USP 750 mg

ANTACID-Dye & Gluten free

Relieves:

- Upset stomach
- Sour stomach
- Acid indigestion

BERRY BLAST

NATURALLY & ARTIFICIALLY FLAVORED

36 CHEWABLE TABLETS

*This product is not manufactured or distributed by GlaxoSmithKline, the distributor of TUMS®.

Distributed by:

CVS Pharmacy,Inc.

One CVS Drive,

Woonsocket,RI 02895

©2015 CVS/pharmacy

CVS.com®

1-800-SHOP CVS

Made in USA

CVS® Quality

Money Back Guarantee

GLUTEN FREE